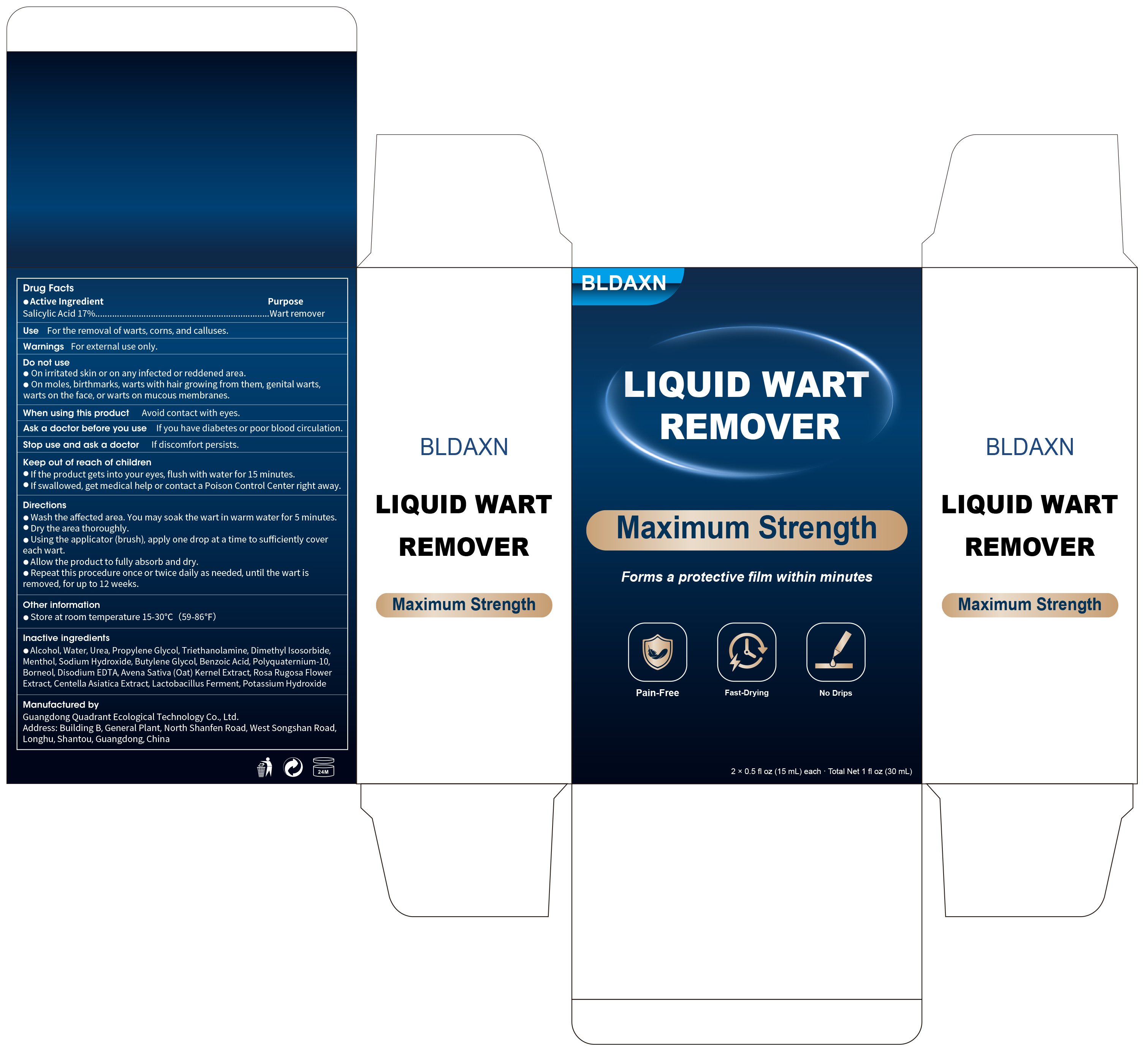 DRUG LABEL: BLDAXN Liquid WART REMOVER
NDC: 76986-024 | Form: LIQUID
Manufacturer: Guangdong Quadrant Ecological Technology Co., Ltd.
Category: otc | Type: HUMAN OTC DRUG LABEL
Date: 20260130

ACTIVE INGREDIENTS: SALICYLIC ACID 0.17 g/1 mL
INACTIVE INGREDIENTS: UREA; WATER; ROSA RUGOSA FLOWER; POLYQUATERNIUM-10 (1000 MPA.S AT 2%); BUTYLENE GLYCOL; TRIETHANOLAMINE; PROPYLENE GLYCOL; ALCOHOL; MENTHOL; DIMETHYL ISOSORBIDE; OAT; EMMENTAL LACTOBACILLUS; BENZOIC ACID; EDETATE DISODIUM; POTASSIUM HYDROXIDE; SODIUM HYDROXIDE; BORNEOL; CENTELLA ASIATICA TRITERPENOIDS

76986-024 BLDAXN LIQUID WART REMOVER

ACTIVE INGREDIENT

SALICYLIC ACID 17%

PURPOSE

Wart remover

INDICATIONS AND USAGE

For the removal of warts, corns, and calluses

WARNINGS

For external use only.

DO NOT USE

On irritated skin or on anyinfected or reddened area.
On moles, birthmarks, warts with hair growing from them, genital warts,warts on the face,or warts on mucous membranes.

When using this product Avoid contact with eyes.
Ask a doctor before you use lf you have diabetes or poor blood circulation.

Stop use and ask a doctor If discomfort persists.

KEEP OUT OF REACH OF CHILDREN

If the product gets into your eyes, flush with water for 15 minutes.
If swallowed, get medical help or contact a Poison Control Center right away.

DOSAGE AND ADMINISTRATION

Wash the affected area. You may soak the wart in warm water for 5 minutes.
Dry the area thoroughly.
Using the applicator (brush), apply one drop at a time to sufficiently cover each wart.
Allow the product to fully absorb and dry.
Repeat this procedure once or twice daily as needed, until the wart is removed, for up to 12 weeks.

INACTIVE INGREDIENT

ALCOHOL
UREA
PROPYLENE GLYCOL
WATER
TRIETHANOLAMINE
DIMETHYL ISOSORBIDE
MENTHOL
CENTELLA ASIATICA EXTRACT
AVENA SATIVA (OAT) KERNEL EXTRACT
ROSA RUGOSA FLOWER EXTRACT
LACTOBACILLUS FERMENT
BUTYLENE GLYCOL
WATER
SODIUM HYDROXIDE
BENZOIC ACID
POLYQUATERNIUM-10
BORNEOL
DISODIUM EDTA
POTASSIUM HYDROXIDE